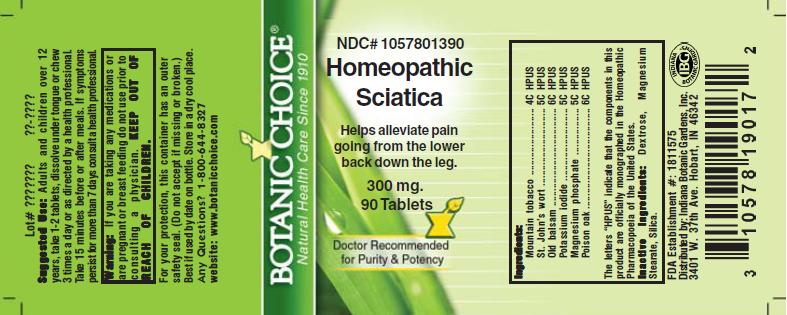 DRUG LABEL: Homeopathic Sciatica Formula
NDC: 10578-013 | Form: TABLET
Manufacturer: Indiana Botanic Gardens
Category: homeopathic | Type: HUMAN OTC DRUG LABEL
Date: 20110325

ACTIVE INGREDIENTS: ARNICA MONTANA 4 [hp_C]/1 1; HYPERICUM PERFORATUM 5 [hp_C]/1 1; PSEUDOGNAPHALIUM LUTEOALBUM LEAF 6 [hp_C]/1 1; POTASSIUM IODIDE 5 [hp_C]/1 1; MAGNESIUM PHOSPHATE, DIBASIC TRIHYDRATE 5 [hp_C]/1 1; TOXICODENDRON PUBESCENS LEAF 6 [hp_C]/1 1
INACTIVE INGREDIENTS: DEXTROSE; MAGNESIUM STEARATE ; SILICON DIOXIDE 

Homeopathic Sciatica Formula

ACTIVE INGREDIENT

I n g r e d i e n t s :

Mountain tobacco.......................... 4C HPUS
St. John's wort................. 5C HPUS
Old balsam............................... 6C HPUS
Potassium iodide.............................. 5C HPUS
Magnesium phosphate................ 5C HPUS
Poison oak.................... 6C HPUS

The letters “HPUS” indicate that the components in
this product are officially monographed in the
Homeopathic Pharmacopoeia of the United States.

PURPOSE

Helps alleviate pain going from the lower back down the leg

KEEP OUT OF
REACH OF CHILDREN.

INDICATIONS AND USAGE

Helps alleviate pain going from the lower back down the leg

WARNINGS

Warning: If you are taking any medications or
are pregnant or breast feeding do not use prior to
consulting a physician.

DOSAGE AND ADMINISTRATION

Suggested Use: Adults and children over 12
years, take 1-2 tablets, dissolve under tongue or
chew 3 times a day or as directed by a health care
professional. Take 15 minutes before or after meals.
If symptoms persist for more than 7 days consult a
health professional.

Inactive Ingredients: Dextrose, Magnesium
Stearate, Silica.

PACKAGE LABEL

NDC# 1057801390

Homeopathic Sciatica Formula

Helps alleviate pain going from the lower back down the leg

300 mg.
90 Tablets

USER SAFETY WARNINGS

For your protection, this container has an outer
safety seal. (Do not accept if missing or broken.)
Best if used by date on bottle. Store in a dry cool place.
Any Questions? 1-800-644-8327
website: www.botanicchoice.com

FDA Establishment #: 1811575

Distributed by: Indiana Botanic Gardens, Inc.
3401 W. 37th Ave. Hobart, IN 46342